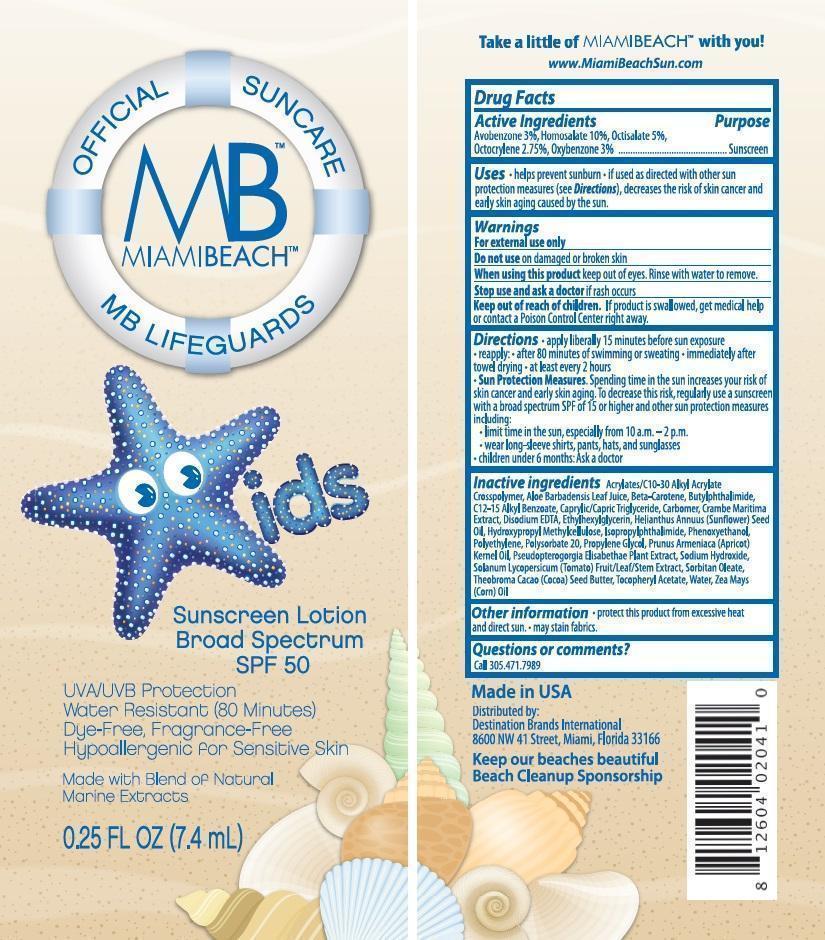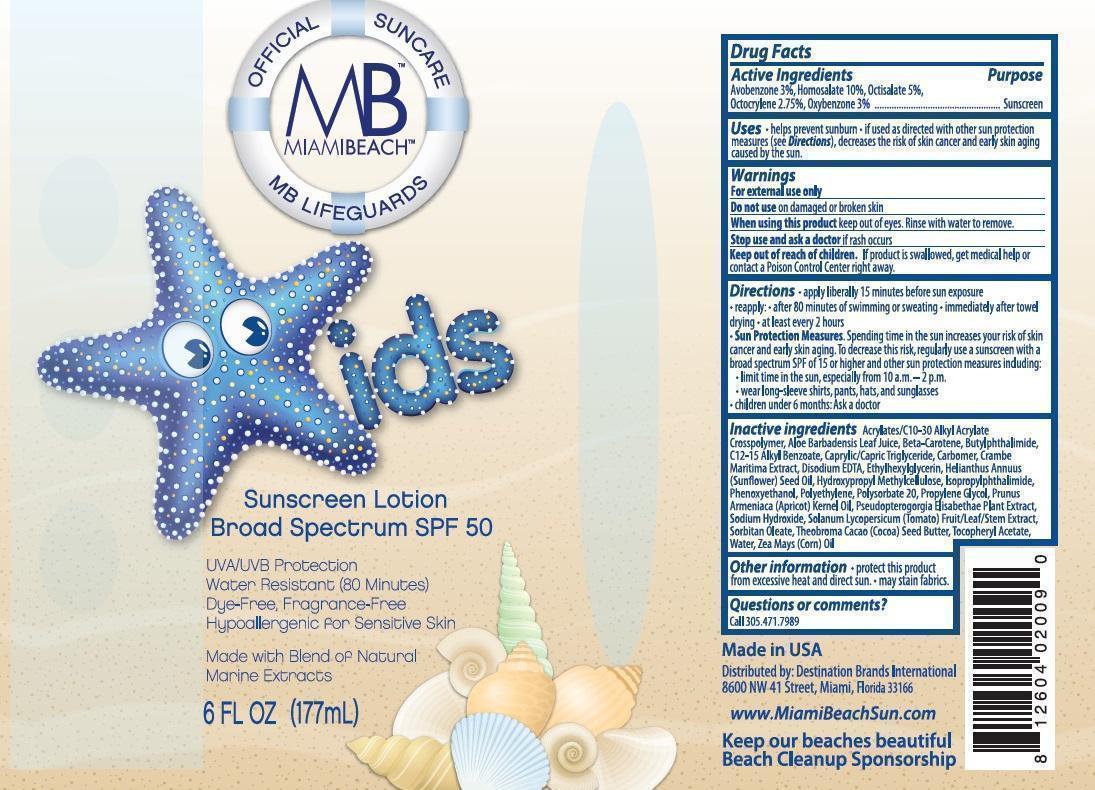 DRUG LABEL: BLI Holdings
NDC: 58443-0147 | Form: LOTION
Manufacturer: Prime Enterprises, Inc.
Category: otc | Type: HUMAN OTC DRUG LABEL
Date: 20200117

ACTIVE INGREDIENTS: AVOBENZONE 29.7 mg/1 mL; HOMOSALATE 99 mg/1 mL; OCTISALATE 49.5 mg/1 mL; OCTOCRYLENE 27.225 mg/1 mL; OXYBENZONE 29.7 mg/1 mL
INACTIVE INGREDIENTS: (C10-C30)ALKYL METHACRYLATE ESTER; CARBOMER COPOLYMER TYPE B (ALLYL PENTAERYTHRITOL CROSSLINKED); ALOE VERA LEAF; N-BUTYLPHTHALIMIDE; ISOPROPYLPHTHALIMIDE; ALKYL (C12-15) BENZOATE; CAPRYLIC/CAPRIC ACID; CRAMBE MARITIMA LEAF; CARBOMER HOMOPOLYMER TYPE C (ALLYL PENTAERYTHRITOL CROSSLINKED); EDETATE DISODIUM; HELIANTHUS ANNUUS SEED WAX; HYPROMELLOSES; PHENOXYETHANOL; ETHYLHEXYLGLYCERIN; HIGH DENSITY POLYETHYLENE; POLYSORBATE 20; PROPYLENE GLYCOL; PSEUDOPTEROGORGIA ELISABETHAE; .ALPHA.-TOCOPHEROL ACETATE; APRICOT KERNEL OIL; WATER; SOLANUM LYCOPERSICUM; SODIUM HYDROXIDE; PEG-6 SORBITAN OLEATE; COCOA BUTTER; CORN OIL; .BETA.-CAROTENE

Active ingredients

Avobenzone 3 %, Homosalate 10 %, Octisalate 5 %, Octocrylene 2.75 %, and Oxybenzone 3 %

Purpose

Sunscreen

Uses

•helps prevent sunburn •if used as directed with other sun protection measures (see Directions), decreases the risk of skin cancer and early skin aging caused by the sun.

Warnings

OTHER SAFETY INFORMATION

For external use only

Do not use on damaged or broken skin

When using this product keep out of eyes. Rinse with water to remove

Stop use and ask a doctor if rash occurs.

Keep out of reach of children. If product is swallowed, get medical help or contact a Poison Control Center right away.

Directions

- apply liberally 15 minutes before sun exposure
- reapply: •after 80 minutes of swimming or sweating •immediately after towel drying •at least every 2 hours
- Sun Protection Measures. Spending time in the sun increases our risk of skin cancer and earl skin aging. To decrease this risk, regularly use a sunscreen with a broad spectrum SPF of 15 or higher and other sun protection measures including:
  - limit time in the sun, especially from 10 a.m.-2 p.m.
  - wear long-sleeve shirts, pants, hats, and sunglasses
- Children under 6 months: Ask a doctor

Inactive Ingredients

Acrylates/C10-30 Alkyl Acrylate Crosspolymer, Aloe Barbadensis Leaf Juice, Beta-Carotene, Butylphthalimide, C12-15 Alkyl Benzoate, Caprylic/ Capric Triglyceride, Carbomer, Crambe Maritima Extract, Disodium EDTA, Ethylhexyglycerin, Helianthus Annuus (Sunflower) Seed Oil, Hydroxypropyl Methylcellulose, Isopropylphthalimide, Phenoxyethanol, Polyethylene, Polysorbate 20, Propylene Glycol, Propylene Glycol, Prunus Ameniaca (Apricot) Kernel Oil, Pseudopterogorgia Elisabethae Plant Extract, Sodium Hydroxide, Solanum Lycopersicum (Tomato) Fruit/Leaf/Steam Extract, Sorbitan Oleate, Theobroma Cacao (Cocoa) Seed Butter, Tocopheryl Acetate, Water (Aqua), Zea Mays (Corn) Oil

Other information

- protect this product from excesive heat and direct sun. •may stain fabrics.

Questions or Comments?

Call 305.471.7989

PRINCIPAL DISPLAY PANEL - 177 mL Bottle Label

OFFICIAL SUNCARE

MB

MIAMIBEACH

MB LIFEGUARDS

KIDS

Sunscreen Lotion

Broad Spectrum SPF 50

UVA/UVB Protection

Water Resistant (80 Minutes)

Dye-Free, Fragrance-Free

Hypoallergenic for Sensitive Skin

Made with Blend of Natural

Marine Extracts

6 FL OZ (177mL)

OFFICIAL SUNCARE

MB

MIAMIBEACH

MB LIFEGUARDS

KIDS

Sunscreen Lotion

Broad Spectrum

SPF 50

UVA/UVB Protection

Water Resistant (80 Minutes)

Dye-Free, Fragrance-Free

Hypoallergenic for Sensitive Skin

Made with Blend of Natural

Marine Extracts

0.25 FL OZ (7.4mL)